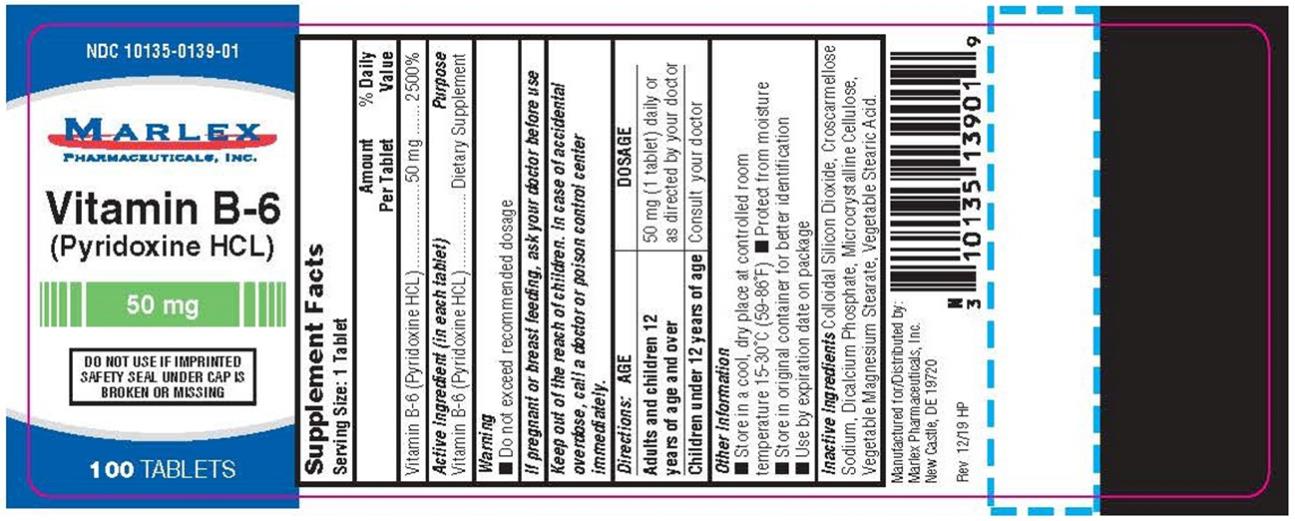 DRUG LABEL: B-6 Pyridoxine HCL
NDC: 10135-139 | Form: TABLET
Manufacturer: Marlex Pharmaceuticals Inc
Category: other | Type: DIETARY SUPPLEMENT
Date: 20200128

ACTIVE INGREDIENTS: PYRIDOXINE HYDROCHLORIDE 50 mg/1 1
INACTIVE INGREDIENTS: MICROCRYSTALLINE CELLULOSE; ANHYDROUS DIBASIC CALCIUM PHOSPHATE; SILICON DIOXIDE; CROSCARMELLOSE SODIUM; STEARIC ACID; MAGNESIUM STEARATE

B-6 Pyridoxine HCL Tablets

Supplement Facts

Serving Size: 1 Tablet
 | Amount per Tablet | % Daily Value
Vitamin B-6 (Pyridoxine HCL) | 50 mg | 2500%
Active Ingredient (in each tablet) |  | Purpose
Vitamin B-6 (Pyridoxine HCL) |  | Dietary Supplement

Warning:

- Do not exceed recommended dosage.

If pregnant or breast-feeding,

ask your doctor before use.

Keep out of the reach of children.

In case of accidental overdose, call a doctor or poison control center immediately.

Directions

Adults and Children 18 years and over:

50 mg (1 tablet) daily or as directed by your doctor

Children under 12 years of age:

Consult your doctor

Other Information:

- Store in a cool, dry place at controlled room temperature 15-30ºC (59-86ºF)
- Protect from moisture
- Store in original container for better identification
- Use by expiration date on package

Inactive Ingredients:

Microcrystalline Cellulose, Dicalcium Phosphate, vegetable Stearic Acid, Colloidal Silicon Dioxide, Vegetable Magnesium Stearate, Croscarmellose Sodium.

Manufactured for/Distributed by:
Marlex Pharmaceuticals, Inc.,
New Castle, DE 19720

Rev. 12/19 HP

PRINCIPAL DISPLAY PANEL

NDC 10135-0139-01
Vitamin B-6
(Pyridoxine HCL)
50 mg
100 Tablets